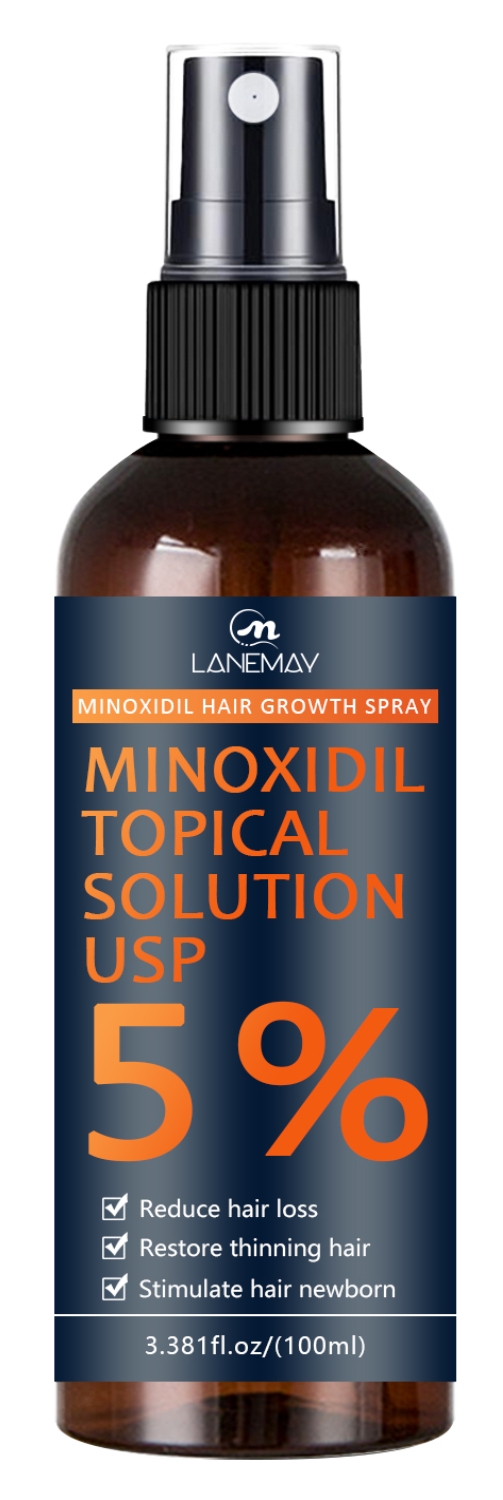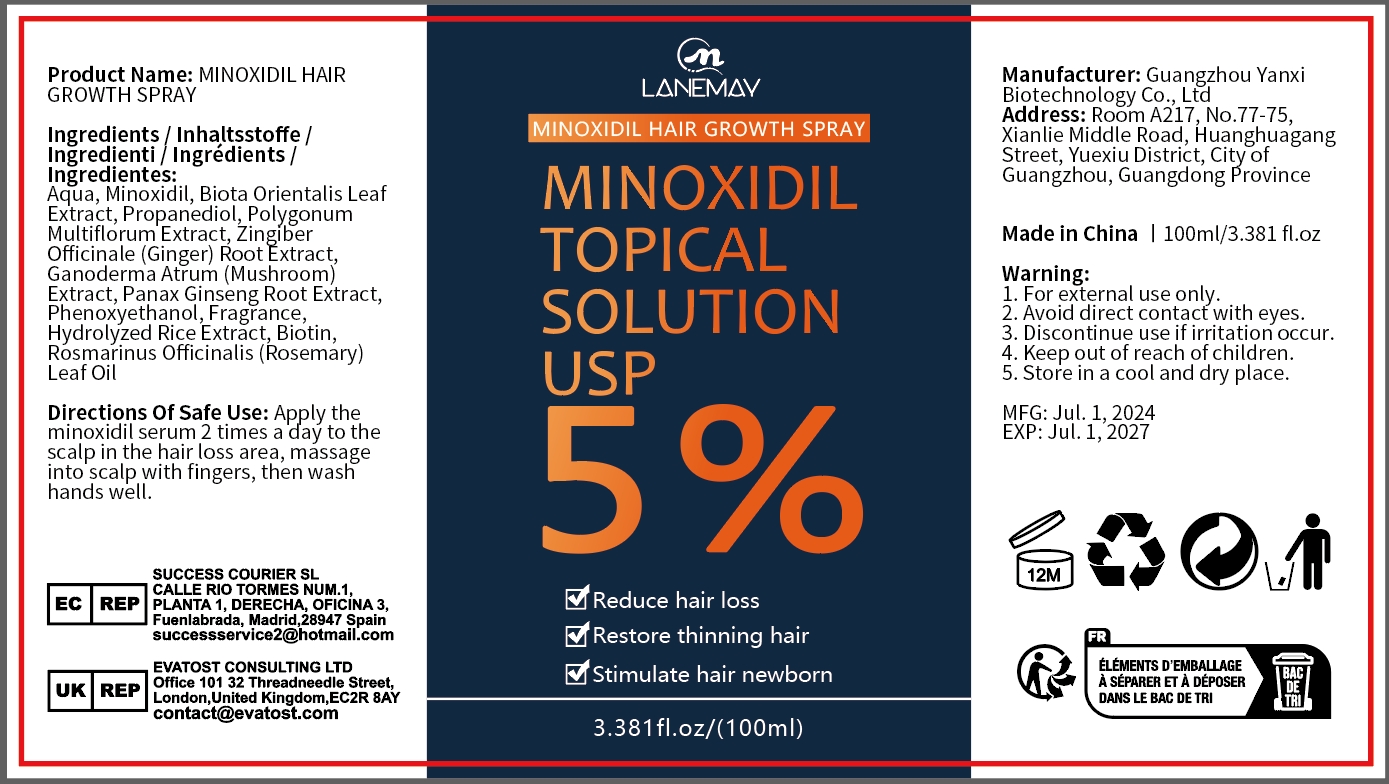 DRUG LABEL: Minoxidil Hair GrowthSpray
NDC: 84025-188 | Form: SPRAY
Manufacturer: Guangzhou Yanxi Biotechnology Co.. Ltd
Category: otc | Type: HUMAN OTC DRUG LABEL
Date: 20240912

ACTIVE INGREDIENTS: PHENOXYETHANOL 3 mg/100 mL; MINOXIDIL 5 mg/100 mL
INACTIVE INGREDIENTS: WATER

DOSAGE AND ADMINISTRATION

Spray for treating hair loss and promoting hair growth

WARNINGS

keep out of children

INACTIVE INGREDIENT

AUQA

INDICATIONS AND USAGE

For daily hair care

keep out of children

PURPOSE

Effectively improve hair loss and keep hair healthy